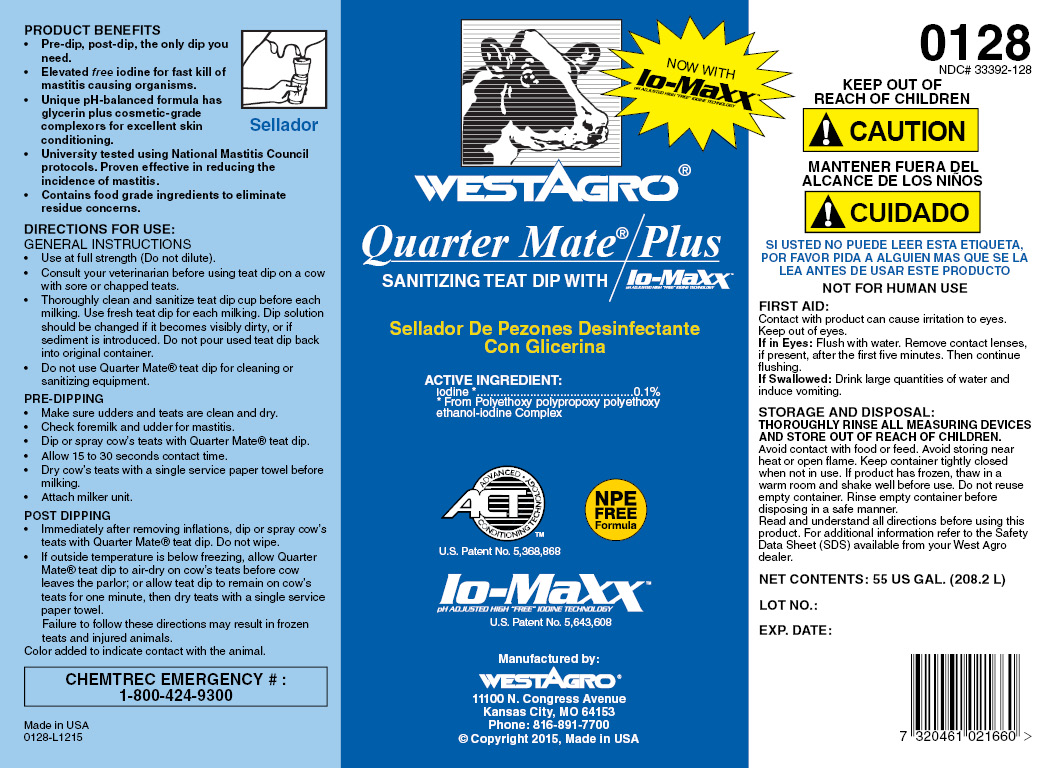 DRUG LABEL: QuarterMate
NDC: 33392-128 | Form: SOLUTION
Manufacturer: WestAgro, Inc.
Category: animal | Type: OTC ANIMAL DRUG LABEL
Date: 20230912

ACTIVE INGREDIENTS: Iodine 0.1 kg/100 kg
INACTIVE INGREDIENTS: FD&C BLUE NO. 1; SODIUM HYDROXIDE; ANHYDROUS CITRIC ACID; POLOXAMER 335; GLYCERIN; XANTHAN GUM; POLOXAMER 403; water; SODIUM CHLORIDE; FD&C RED NO. 40; FD&C YELLOW NO. 5; SODIUM IODIDE; DOCUSATE SODIUM; SODIUM IODATE

WESTAGRO QUARTERMATE/PLUS

SANITIZING TEAT DIP WITH / Io-MaXX
pH ADJUSTED HIGH "FREE" IODINE TECHNOLOGY

Sellador De Pezones Desinfectante Con Glicerina

ACTIVE INGREDIENT:
Iodine ........................................... 0.1%
From Polyethoxy polypropoxy polyethoxy ethanol-iodine Complex

ACT
ADVANCED CONDITIONING TECHNOLOGY

U.S. Patent No.
5,368,868

NPE FREE Formula

Io-MaXX
pH ADJUSTED HIGH "FREE" IODINE TECHNOLOGY
U.S. Patent No. 5,643,608

Manufactured by:
WESTAGRO
11100 N. Congress Ave. Kansas City, MO
64153-1296

PRODUCT BENEFITS

- Pre-dip, post-dip, the only dip you need.
- Elevated free iodine for fast kill of mastitis causing organisms.
- Unique pH-balanced formula has glycerin plus cosmetic-grade complexors for excellent skin conditioning.
- University tested using National Mastitis Council protocols. Proven effective in reducing the incidence of mastitis.
- Contains food grade ingredients to eliminate residue concerns.

INDICATIONS AND USAGE

DIRECTIONS FOR USE:
GENERAL INSTRUCTIONS

- Use at full strength (Do not dilute).
- Consult your veterinarian before using teat dip on a cow with sore or chapped teats.
- Thoroughly clean and sanitize teat dip cup before each milking. Use fresh teat dip for each milking. Dip solution should be changed if it becomes visibly dirty, or if sediment is introduced. Do not pour used teat dip back into original container.
- Do not use Quarter Mate teat dip for cleaning or sanitizing equipment.

PRE-DIPPING

- Make sure udder and teats are clean and dry.
- Check foremilk and udder for mastitis.
- Dip or spray cow's teats with Quarter Mate teat dip.
- Allow 15 to 30 seconds contact time.
- Dry cow's teats with a single service paper towel before milking.
- Attach milker unit.

POST DIPPING

- Immediately after removing inflations, dip or spray cow's teats with Quarter Mate teat dip. Do not wipe.
- If outside temperature is below freezing, allow Quarter Mate teat dip to air-dry on cow's teats before cow leaves the parlor; or allow teat dip to remain on cow's teats for one minute, then dry teats with single service paper towel.

Failure to follow these directions may result in frozen teats and injured animals.

Color added to indicate contact with the animal.

Made in U.S.A.
0128-I0506
Copyright 2006, West Agro, Inc.

NOW WITH

Io-MaXX
pH ADJUSTED "FREE" IODINE TECHNOLOGY

0128
NDC 33392-128

KEEP OUT OF REACH OF CHILDREN

! CAUTION

MANTENER FUERA DEL ALCANCE DE LOS NINOS

! CUIDADO

SI USTED NO PUEDE LEER ESTA ETIQUETA, POR FAVOR PIDA A ALGUIEN MAS QUE SE LA LEA ANTES DE USAR ESTE PRODUCTO

FIRST AID

Contact with product can cause irritation to eyes. Keep out of eyes.
Eye Contact: Flush with water. Remove contact lenses, if present, after the first five minutes. Then continue flushing.
If Swallowed: Drink large quantities of water and induce vomiting.

STORAGE AND DISPOSAL:

THOROUGHLY RINSE ALL MEASURING DEVICES AND STORE OUT OF REACH OF CHILDREN. Avoid contact with food or feed. Avoid storing near heat or open flame. Keep container tightly closed when not in use. If product has frozen, thaw in a warm room and shake well before use. Do not reuse empty container. Rinse empty container before disposing in a safe manner.

Read and understand all directions before using this product. For additional information refer to the Material Safety Data Sheet (MSDS) available from your West Agro dealer.

CHEMTREC EMERGENCY NO. 1-800-424-9300

NET
CONTENTS:

LOT NO:

EXPIRATION DATE: